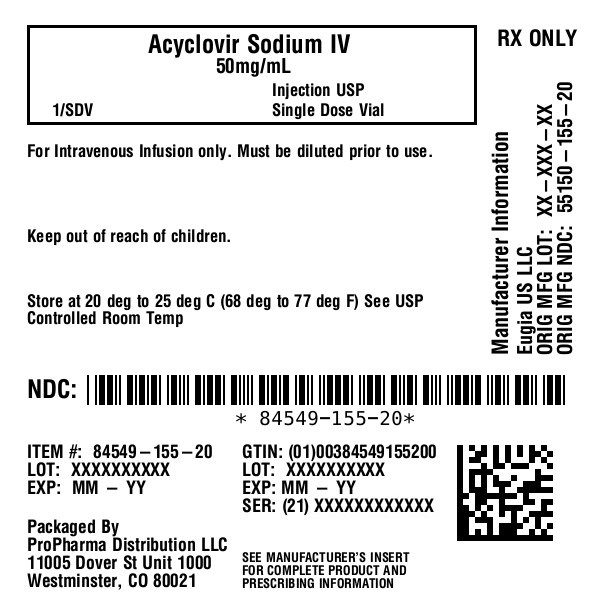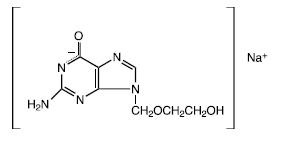 DRUG LABEL: Acyclovir Sodium
NDC: 84549-155 | Form: INJECTION, SOLUTION
Manufacturer: ProPharma Distribution
Category: prescription | Type: HUMAN PRESCRIPTION DRUG LABEL
Date: 20250718

ACTIVE INGREDIENTS: ACYCLOVIR SODIUM 1000 mg/20 mL
INACTIVE INGREDIENTS: WATER

FOR INTRAVENOUS INFUSION ONLY
Rx only

DESCRIPTION

Acyclovir Sodium Injection is a synthetic nucleoside analog, active against herpes viruses. It is a sterile, aqueous solution for intravenous infusion, containing 50 mg acyclovir per mL in Water for Injection, USP. The concentration is equivalent to 54.9 mg of acyclovir sodium per mL in Water for Injection, USP. The sodium content is approximately 5.1 mg/mL. The pH range of the solution is 10.85 to 11.50. Further dilution of Acyclovir Sodium Injection in an appropriate intravenous solution must be performed before infusion (see DOSAGE AND ADMINISTRATION, Administration).
The chemical name of acyclovir sodium is 9-[(2-Hydroxyethoxy)methyl] guanine, and has the following structural formula:

Acyclovir USP is a white to off-white, crystalline powder. Acyclovir sodium is the sodium salt of acyclovir, which is formed in situ, with the molecular formula C8H10N5NaO3and a molecular weight of 247.19. The maximum solubility in water at 25°C exceeds 100 mg/mL. At physiologic pH, acyclovir sodium exists as the unionized form with a molecular weight of 225 and a maximum solubility in water at 37°C of 2.5 mg/mL. The pka’s of acyclovir are 2.27 and 9.25.

VIROLOGY

Mechanism of Antiviral Action

Acyclovir is a synthetic purine nucleoside analogue with in vitroand in vivoinhibitory activity against herpes simplex virus types 1 (HSV-1), 2 (HSV-2) and varicella-zoster virus (VZV).
The inhibitory activity of acyclovir is highly selective due to its affinity for the enzyme thymidine kinase (TK) encoded by HSV and VZV. This viral enzyme converts acyclovir into acyclovir monophosphate, a nucleotide analogue. The monophosphate is further converted into diphosphate by cellular guanylate kinase and into triphosphate by a number of cellular enzymes. In vitro, acyclovir triphosphate stops replication of herpes viral DNA. This is accomplished in three ways: 1) competitive inhibition of viral DNA polymerase, 2) incorporation into and termination of the growing viral DNA chain, and 3) inactivation of the viral DNA polymerase. The greater antiviral activity of acyclovir against HSV compared to VZV is due to its more efficient phosphorylation by the viral TK.

Antiviral Activities

The quantitative relationship between the in vitrosusceptibility of herpes viruses to antivirals and the clinical response to therapy has not been established in humans, and virus sensitivity testing has not been standardized. Sensitivity testing results, expressed as the concentration of drug required to inhibit by 50% the growth of virus in cell culture (IC50), vary greatly depending upon a number of factors. Using plaque-reduction assays, the IC50 against herpes simplex virus isolates ranges from 0.02 to 13.5 mcg/mL for HSV-1 and from 0.01 to 9.9 mcg/mL for HSV-2. The IC50for acyclovir against most laboratory strains and clinical isolates of VZV ranges from 0.12 to 10.8 mcg/mL. Acyclovir also demonstrates activity against the Oka vaccine strain of VZV with a mean IC50of 1.35 mcg/mL.

Drug Resistance

Resistance of HSV and VZV to acyclovir can result from qualitative or quantitative changes in the viral TK and/or DNA polymerase. Clinical isolates of HSV and VZV with reduced susceptibility to acyclovir have been recovered from immunocompromised patients, especially with advanced HIV infection. While most of the acyclovir-resistant mutants isolated thus far from such patients have been found to be TK-deficient mutants, other mutants involving the viral TK gene (TK partial and TK altered) and DNA polymerase have been isolated. TK-negative mutants may cause severe disease in infants and immunocompromised adults. The possibility of viral resistance to acyclovir should be considered in patients who show poor clinical response during therapy.

CLINICAL PHARMACOLOGY

Pharmacokinetics

The pharmacokinetics of acyclovir after intravenous administration have been evaluated in adult patients with normal renal function during Phase 1/2 studies after single doses ranging from 0.5 to 15 mg/kg and after multiple doses ranging from 2.5 to 15 mg/kg every 8 hours. Proportionality between dose and plasma levels is seen after single doses or at steady-state after multiple dosing. Average steady-state peak and trough concentrations from 1-hour infusions administered every 8 hours are given in Table 1.

Table 1: Acyclovir Peak and Trough Concentrations at Steady-State
Dosage Regimen | CSSmax | CSStrough
5 mg/kg q 8 h (n = 8) | 9.8 mcg/mL range: 5.5 to 13.8 | 0.7 mcg/mL range: 0.2 to 1
10 mg/kg q 8 h (n = 7) | 22.9 mcg/mL range: 14.1 to 44.1 | 1.9 mcg/mL range: 0.5 to 2.9

Concentrations achieved in the cerebrospinal fluid are approximately 50% of plasma values. Plasma protein binding is relatively low (9% to 33%) and drug interactions involving binding site displacement are not anticipated.
Renal excretion of unchanged drug is the major route of acyclovir elimination accounting for 62% to 91% of the dose. The only major urinary metabolite detected is 9-carboxymethoxymethylguanine accounting for up to 14.1% of the dose in patients with normal renal function.
The half-life and total body clearance of acyclovir are dependent on renal function as shown in Table 2.

Table 2: Acyclovir Half-life and Total Body Clearance
Creatinine Clearance (mL/min/1.73 m^2) | Half-Life (hr) | Total Body Clearance
Creatinine Clearance (mL/min/1.73 m^2) | Half-Life (hr) | (mL/min/1.73 m^2) | (mL/min/kg)
>80 | 2.5 | 327 | 5.1
50 to 80 | 3 | 248 | 3.9
15 to 50 | 3.5 | 190 | 3.4
0 (Anuric) | 19.5 | 29 | 0.5

Special Populations

Adults With Impaired Renal Function

Acyclovir was administered at a dose of 2.5 mg/kg to 6 adult patients with severe renal failure. The peak and trough plasma levels during the 47 hours preceding hemodialysis were 8.5 mcg/mL and 0.7 mcg/mL, respectively.
Consult DOSAGE AND ADMINISTRATIONsection for recommended adjustments in dosing based upon creatinine clearance.

Pediatrics

Acyclovir pharmacokinetics were determined in 16 pediatric patients with normal renal function ranging in age from 3 months to 16 years at doses of approximately 10 mg/kg and 20 mg/kg every 8 hours (Table 3). Concentrations achieved at these regimens are similar to those in adults receiving 5 mg/kg and 10 mg/kg every 8 hours, respectively (Table 1). Acyclovir pharmacokinetics were determined in 12 patients ranging in age from birth to 3 months at doses of 5 mg/kg, 10 mg/kg, and 15 mg/kg every 8 hours (Table 3).

Table 3: Acyclovir Pharmacokinetics in Pediatric Patients (Mean ±SD)
Parameter | Birth to 3 Months of Age (n = 12) | 3 Months to 12 Years of Age (n = 16)
CL (mL/min/kg) | 4.46 ± 1.61 | 8.44 ± 2.92
VDSS (L/kg) | 1.08 ± 0.35 | 1.01 ± 0.28
Elimination half-life (hours) | 3.8 ± 1.19 | 2.36 ± 0.97

Geriatrics

Acyclovir plasma concentrations are higher in geriatric patients compared to younger adults, in part due to age-related changes in renal function. Dosage reduction may be required in geriatric patients with underlying renal impairment (see PRECAUTIONS, Geriatric Use).

Drug Interactions

Coadministration of probenecid with acyclovir has been shown to increase the mean acyclovir half-life and the area under the concentration-time curve. Urinary excretion and renal clearance were correspondingly reduced.

Clinical Trials

Herpes Simplex Infections in Immunocompromised Patients

A multicenter trial of acyclovir at a dose of 250 mg/m^2 every 8 hours (750 mg/m^2/day) for 7 days was conducted in 98 immunocompromised patients (73 adults and 25 children) with orofacial, esophageal, genital and other localized infections (52 treated with acyclovir and 46 with placebo). Acyclovir decreased virus excretion, reduced pain, and promoted healing of lesions.

Initial Episodes of Herpes Genitalis

In placebo-controlled trials, 58 patients with initial genital herpes were treated with intravenous acyclovir 5 mg/kg or placebo (27 patients treated with acyclovir and 31 treated with placebo) every 8 hours for 5 days. Acyclovir decreased the duration of viral excretion, new lesion formation, and duration of vesicles, and promoted healing of lesions.

Herpes Simplex Encephalitis

Sixty-two patients ages 6 months to 79 years with brain biopsy-proven herpes simplex encephalitis were randomized to receive either acyclovir (10 mg/kg every 8 hours) or vidarabine (15 mg/kg/day) for 10 days (28 were treated with acyclovir and 34 with vidarabine). Overall mortality at 12 months for patients treated with acyclovir was 25% compared to 59% for patients treated with vidarabine. The proportion of patients treated with acyclovir functioning normally or with only mild sequelae (e.g., decreased attention span) was 32% compared to 12% of patients treated with vidarabine.
Patients less than 30 years of age and those who had the least severe neurologic involvement at time of entry into study had the best outcome with treatment with acyclovir. An additional controlled study performed in Europe demonstrated similar findings.

Neonatal Herpes Simplex Virus Infection

Two hundred and two infants with neonatal herpes simplex infections were randomized to receive either acyclovir 10 mg/kg every 8 hours (n = 107) or vidarabine 30 mg/kg/day (n = 95) for 10 days. Outcomes are presented in Table 4.

Table 4: Mortality at 1 Year
HSV Disease Classification | Treatment Group
HSV Disease Classification | Acyclovir (n = 107) | Vidarabine (n = 95)
SEM* (n = 85) | 0/54 | 0/31
CNS†(n = 71) | 5/35 | 5/36
DISS‡(n = 46) | 11/18 | 14/28
* SEM refers to localized infection with disease limited to skin, eye, and/or mouth.
†CNS refers to infection of the central nervous system with compatible neurologic and CSF
findings.
‡DISS refers to visceral organ involvement such as hepatitis or pneumonitis with or without
CNS involvement.

Rates of neurologic sequelae at 1 year were comparable between the treatment groups.

Varicella-Zoster Infections in Immunocompromised Patients

A multicenter trial of acyclovir at a dose of 500 mg/m^2every 8 hours for 7 days was conducted in immunocompromised patients with zoster infections (shingles). Ninety-four (94) patients were evaluated (52 patients were treated with acyclovir and 42 with placebo). Acyclovir was superior to placebo as measured by reductions in cutaneous dissemination and visceral dissemination.

INDICATIONS AND USAGE

Herpes Simplex Infections in Immunocompromised Patients

Acyclovir Sodium Injection is indicated for the treatment of initial and recurrent mucosal and cutaneous herpes simplex (HSV-1 and HSV-2) in immunocompromised patients.

Initial Episodes of Herpes Genitalis

Acyclovir Sodium Injection is indicated for the treatment of severe initial clinical episodes of herpes genitalis in immuno-competent patients.

Herpes Simplex Encephalitis

Acyclovir Sodium Injection is indicated for the treatment of herpes simplex encephalitis.

Neonatal Herpes Simplex Virus Infection

Acyclovir Sodium Injection is indicated for the treatment of neonatal herpes infections.

Varicella-Zoster Infections in Immunocompromised Patients

Acyclovir Sodium Injection is indicated for the treatment of varicella-zoster (shingles) infections in immunocompromised patients.

CONTRAINDICATIONS

Acyclovir Sodium Injection is contraindicated for patients who develop hypersensitivity to acyclovir or valacyclovir.

WARNINGS

Acyclovir Sodium Injection is intended for intravenous infusion only, and should not be administered topically, intramuscularly, orally, subcutaneously, or in the eye. Intravenous infusions must be given over a period of at least 1 hour to reduce the risk of renal tubular damage (see PRECAUTIONSand DOSAGE AND ADMINISTRATION).
Renal failure, in some cases resulting in death, has been observed with acyclovir therapy (see ADVERSE REACTIONS, Observed During Clinical Practiceand OVERDOSAGE). Thrombotic thrombocytopenic purpura/hemolytic uremic syndrome (TTP/HUS), which has resulted in death, has occurred in immunocompromised patients receiving acyclovir therapy.

PRECAUTIONS

General

Precipitation of acyclovir crystals in renal tubules can occur if the maximum solubility of free acyclovir (2.5 mg/mL at 37°C in water) is exceeded or if the drug is administered by bolus injection. Ensuing renal tubular damage can produce acute renal failure.
Abnormal renal function (decreased creatinine clearance) can occur as a result of acyclovir administration and depends on the state of the patient’s hydration, other treatments, and the rate of drug administration. Concomitant use of other nephrotoxic drugs, pre-existing renal disease, and dehydration make further renal impairment with acyclovir more likely.
Administration of acyclovir by intravenous infusion must be accompanied by adequate hydration.
When dosage adjustments are required, they should be based on estimated creatinine clearance (see DOSAGE AND ADMINISTRATION).
Approximately 1% of patients receiving intravenous acyclovir have manifested encephalopathic changes characterized by either lethargy, obtundation, tremors, confusion, hallucinations, agitation, seizures, or coma. Acyclovir should be used with caution in those patients who have underlying neurologic abnormalities and those with serious renal, hepatic, or electrolyte abnormalities, or significant hypoxia.

Drug Interactions

See CLINICAL PHARMACOLOGY, Pharmacokinetics.

Carcinogenesis, Mutagenesis, Impairment of Fertility

The data presented below include references to peak steady-state plasma acyclovir concentrations observed in humans treated with 30 mg/kg/day (10 mg/kg every 8 hours, dosing appropriate for treatment of herpes zoster or herpes encephalitis), or 15 mg/kg/day (5 mg/kg every 8 hours, dosing appropriate for treatment of primary genital herpes or herpes simplex infections in immunocompromised patients). Plasma drug concentrations in animal studies are expressed as multiples of human exposure to acyclovir at the higher and lower dosing schedules (see CLINICAL PHARMACOLOGY, Pharmacokinetics).
Acyclovir was tested in lifetime bioassays in rats and mice at single daily doses of up to 450 mg/kg administered by gavage. There was no statistically significant difference in the incidence of tumors between treated and control animals, nor did acyclovir shorten the latency of tumors. At 450 mg/kg/day, plasma concentrations in both the mouse and rat bioassay were lower than concentrations in humans.
Acyclovir was tested in 16 in vitroand in vivogenetic toxicity assays. Acyclovir was positive in 5 of the assays.
Acyclovir did not impair fertility or reproduction in mice (450 mg/kg/day, PO) or in rats (25 mg/kg/day, SC). In the mouse study, plasma levels were the same as human levels, while in the rat study, they were 1 to 2 times human levels. At higher doses (50 mg/kg/day, SC) in rats and rabbits (1 to 2 and 1 to 3 times human levels, respectively) implantation efficacy, but not litter size, was decreased. In a rat peri- and post-natal study at 50 mg/kg/day, SC, there was a statistically significant decrease in group mean numbers of corpora lutea, total implantation sites, and live fetuses.
No testicular abnormalities were seen in dogs given 50 mg/kg/day, IV for 1 month (1 to 3 times human levels) or in dogs given 60 mg/kg/day orally for 1 year (the same as human levels). Testicular atrophy and aspermatogenesis were observed in rats and dogs at higher dose levels.

Pregnancy

Teratogenic Effects
Acyclovir administered during organogenesis was not teratogenic in the mouse (450 mg/kg/day, PO), rabbit (50 mg/kg/day, SC and IV), or rat (50 mg/kg/day, SC). These exposures resulted in plasma levels the same as, 4 and 9, and 1 and 2 times, respectively, human levels.
There are no adequate and well-controlled studies in pregnant women. A prospective epidemiologic registry of acyclovir use during pregnancy was established in 1984 and completed in April 1999. There were 749 pregnancies followed in women exposed to systemic acyclovir during the first trimester of pregnancy resulting in 756 outcomes. The occurrence rate of birth defects approximates that found in the general population. However, the small size of the registry is insufficient to evaluate the risk for less common defects or to permit reliable or definitive conclusions regarding the safety of acyclovir in pregnant women and their developing fetuses. Acyclovir should be used during pregnancy only if the potential benefit justifies the potential risk to the fetus.

Nursing Mothers

Acyclovir concentrations have been documented in breast milk in two women following oral administration of acyclovir and ranged from 0.6 to 4.1 times corresponding plasma levels. These concentrations would potentially expose the nursing infant to a dose of acyclovir up to 0.3 mg/kg/day. Acyclovir should be administered to a nursing mother with caution and only when indicated.

Pediatric Use

See DOSAGE AND ADMINISTRATION.

Geriatric Use

Clinical studies of acyclovir did not include sufficient numbers of patients aged 65 and over to determine whether they respond differently than younger patients. Other reported clinical experience has identified differences in the severity of CNS adverse events between elderly and younger patients (see ADVERSE REACTIONS, Observed During Clinical Practice). In general, dose selection for an elderly patient should be cautious, reflecting the greater frequency of decreased renal function, and of concomitant disease or other drug therapy. This drug is known to be substantially excreted by the kidney, and the risk of toxic reactions to this drug may be greater in patients with impaired renal function. Because elderly patients are more likely to have decreased renal function, care should be taken in dose selection, and it may be useful to monitor renal function.

ADVERSE REACTIONS

The adverse reactions listed below have been observed in controlled and uncontrolled clinical trials in approximately 700 patients who received acyclovir at approximately 5 mg/kg (250 mg/m^2) 3 times daily, and approximately 300 patients who received approximately 10 mg/kg (500 mg/m^2) 3 times daily.
The most frequent adverse reactions reported during administration of acyclovir were inflammation or phlebitis at the injection site in approximately 9% of the patients, and transient elevations of serum creatinine or BUN in 5% to 10% (the higher incidence occurred usually following rapid [less than 10 minutes] intravenous infusion). Nausea and/or vomiting occurred in approximately 7% of the patients (the majority occurring in nonhospitalized patients who received 10 mg/kg). Itching, rash, or hives occurred in approximately 2% of patients. Elevation of transaminases occurred in 1% to 2% of patients.
The following hematologic abnormalities occurred at a frequency of less than 1%: anemia, neutropenia, thrombocytopenia, thrombocytosis, leukocytosis, and neutrophilia. In addition, anorexia and hematuria were observed.

Observed During Clinical Practice

In addition to adverse events reported from clinical trials, the following events have been identified during post-approval use of Acyclovir Sodium Injection in clinical practice. Because they are reported voluntarily from a population of unknown size, estimates of frequency cannot be made. These events have been chosen for inclusion due to either their seriousness, frequency of reporting, potential causal connection to acyclovir, or a combination of these factors.
General: Anaphylaxis, angioedema, fatigue, fever, headache, pain, peripheral edema.
Digestive:Abdominal pain, diarrhea, gastrointestinal distress, nausea.
Cardiovascular:Hypotension.
Hematologic and Lymphatic:Disseminated intravascular coagulation, hemolysis, leukocytoclastic vasculitis, leukopenia, lymphadenopathy.
Hepatobiliary Tract and Pancreas:Elevated liver function tests, hepatitis, hyperbilirubinemia, jaundice.
Musculoskeletal:Myalgia.
Nervous:Aggressive behavior, agitation, ataxia, coma, confusion, delirium, dizziness, dysarthria, encephalopathy, hallucinations, obtundation, paresthesia, psychosis, seizure, somnolence, tremor. These symptoms may be marked, particularly in older adults (see PRECAUTIONS).
Skin:Alopecia, erythema multiforme, photosensitive rash, pruritus, rash, Stevens-Johnson syndrome, toxic epidermal necrolysis, urticaria. Severe local inflammatory reactions, including tissue necrosis, have occurred following infusion of acyclovir into extravascular tissues.
Special Senses:Visual abnormalities.

Urogenital:Renal failure, elevated blood urea nitrogen, elevated creatinine (see WARNINGS).

OVERDOSAGE

Overdoses involving ingestions of up to 20 g have been reported. Adverse events that have been reported in association with overdosage include agitation, coma, seizures, and lethargy. Precipitation of acyclovir in renal tubules may occur when the solubility (2.5 mg/mL) is exceeded in the intratubular fluid. Overdosage has been reported following bolus injections or inappropriately high doses, and in patients whose fluid and electrolyte balance were not properly monitored. This has resulted in elevated BUN and serum creatinine, and subsequent renal failure. In the event of acute renal failure and anuria, the patient may benefit from hemodialysis until renal function is restored (see DOSAGE AND ADMINISTRATION).

DOSAGE AND ADMINISTRATION

CAUTION - RAPID OR BOLUS INTRAVENOUS INJECTION MUST BE AVOIDED(see WARNINGS and PRECAUTIONS).
INTRAMUSCULAR OR SUBCUTANEOUS INJECTION MUST BE AVOIDED(see WARNINGS).
Therapy should be initiated as early as possible following onset of signs and symptoms of herpes infections.
A maximum dose equivalent to 20 mg/kg every 8 hours should not be exceeded for any patient.

Dosage

HERPES SIMPLEX INFECTIONS
MUCOSAL AND CUTANEOUS HERPES SIMPLEX (HSV-1 AND HSV-2) INFECTIONS IN IMMUNOCOMPROMISED PATIENTS
Adults and Adolescents (12 years of age and older)
5 mg/kg infused at a constant rate over 1 hour, every 8 hours for 7 days.
Pediatrics (Under 12 years of age)
10 mg/kg infused at a constant rate over 1 hour, every 8 hours for 7 days.
SEVERE INITIAL CLINICAL EPISODES OF HERPES GENITALIS
Adults and Adolescents (12 years of age and older)
5 mg/kg infused at a constant rate over 1 hour, every 8 hours for 5 days.
HERPES SIMPLEX ENCEPHALITIS
Adults and Adolescents (12 years of age and older)
10 mg/kg infused at a constant rate over 1 hour, every 8 hours for 10 days.
Pediatrics (3 months to 12 years of age)
20 mg/kg infused at a constant rate over 1 hour, every 8 hours for 10 days .
Neonatal Herpes Simplex Virus Infections (Birth to 3 months)
10 mg/kg infused at a constant rate over 1 hour, every 8 hours for 10 days. In neonatal herpes simplex infections, doses of 15 mg/kg or 20 mg/kg (infused at a constant rate over 1 hour every 8 hours) have been used; the safety and efficacy of these doses are not known.
VARICELLA-ZOSTER INFECTIONS
ZOSTER IN IMMUNOCOMPROMISED PATIENTS
Adults and Adolescents (12 years of age and older)
10 mg/kg infused at a constant rate over 1 hour, every 8 hours for 7 days.
Pediatrics (Under 12 years of age)
20 mg/kg infused at a constant rate over 1 hour, every 8 hours for 7 days.
Obese Patients
Obese patients should be dosed at the recommended adult dose using Ideal Body Weight.
PATIENTS WITH ACUTE OR CHRONIC RENAL IMPAIRMENT
Refer to DOSAGE AND ADMINISTRATIONsection for recommended doses, and adjust the dosing interval as indicated in Table 5.

Table 5: Dosage Adjustments for Patients with Renal Impairment
Creatinine Clearance (mL/min/1.73 m^2) | Percent of Recommended Dose | Dosing Interval (hours)
>50 | 100% | 8
25 to 50 | 100% | 12
10 to 25 | 100% | 24
0 to 10 | 50% | 24

Hemodialysis

For patients who require dialysis, the mean plasma half-life of acyclovir during hemodialysis is approximately 5 hours. This results in a 60% decrease in plasma concentrations following a six-hour dialysis period. Therefore, the patient’s dosing schedule should be adjusted so that an additional dose is administered after each dialysis.

Peritoneal Dialysis

No supplemental dose appears to be necessary after adjustment of the dosing interval.

Administration

The calculated dose should be further diluted in an appropriate intravenous solution at a volume selected for administration during each 1 hour infusion. Infusion concentrations of approximately 7 mg/mL or lower are recommended. In clinical studies, the average 70 kg adult received between 60 and 150 mL of fluid per dose. Higher concentrations (e.g., 10 mg/mL) may produce phlebitis or inflammation at the injection site upon inadvertent extravasation. Standard, commercially available electrolyte and glucose solutions are suitable for intravenous administration; biologic or colloidal fluids (e.g., blood products, protein solutions, etc.) are not recommended.
Once diluted for administration, each dose should be used within 24 hours.
Parenteral drug products should be inspected visually for particulate matter and discoloration prior to administration, whenever solution and container permit.

HOW SUPPLIED

NDC 84549-155-20 - 1 Single Dose Vial, 20mL